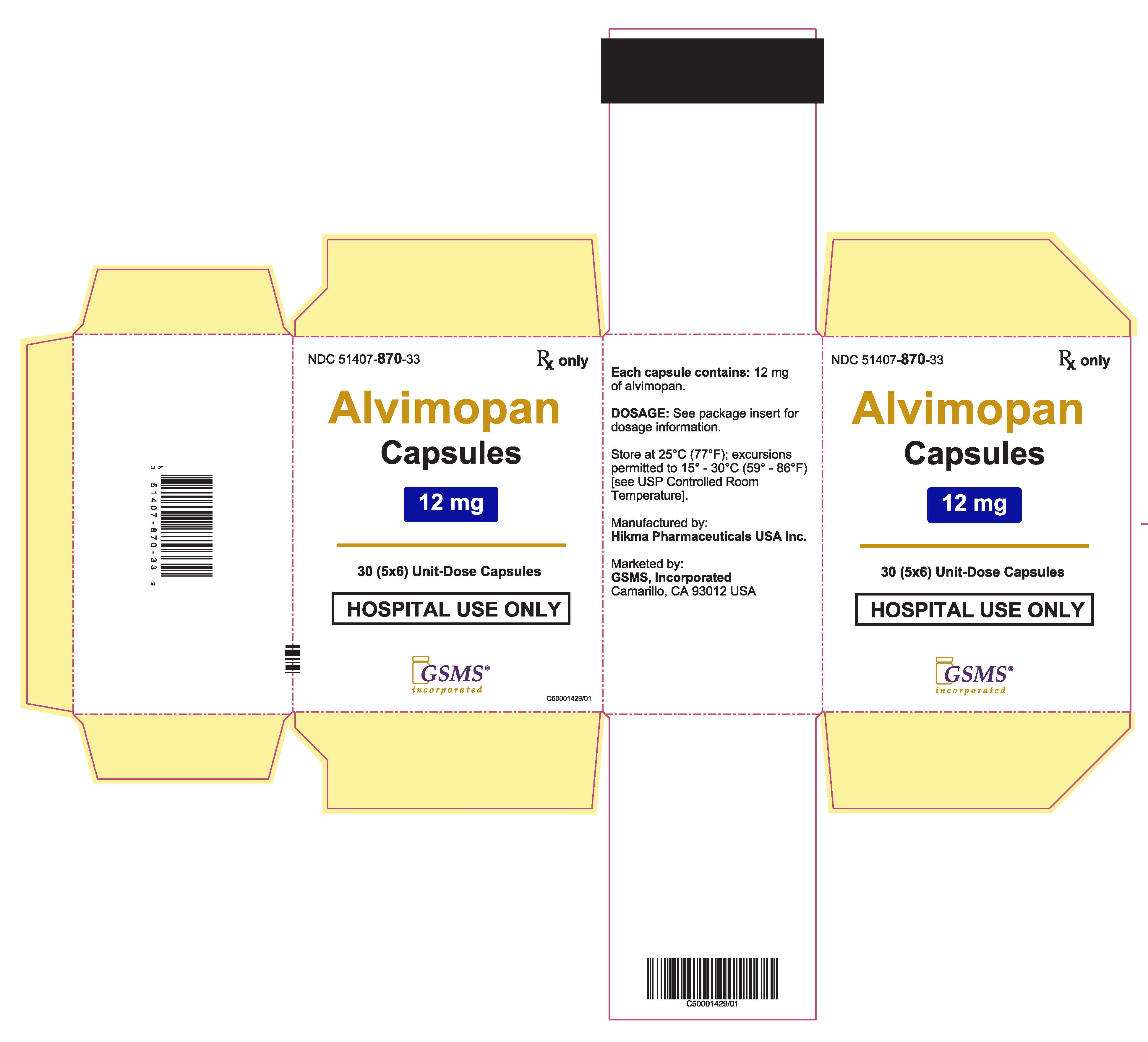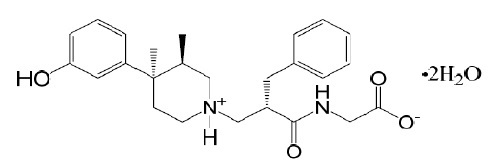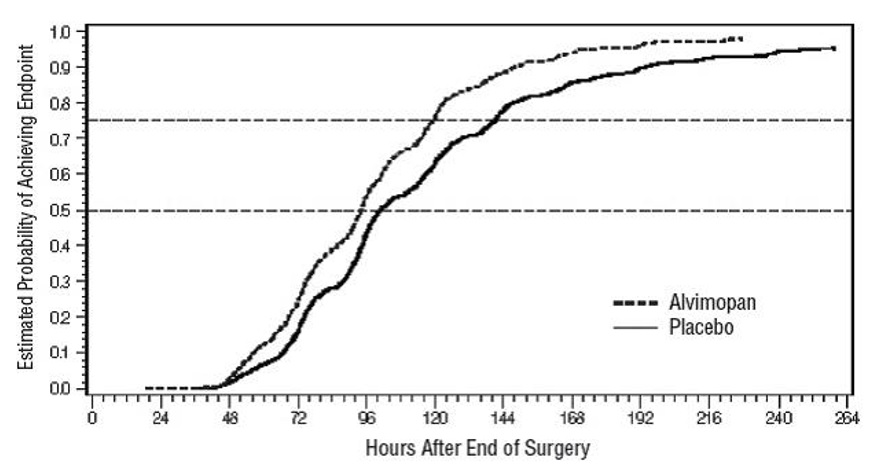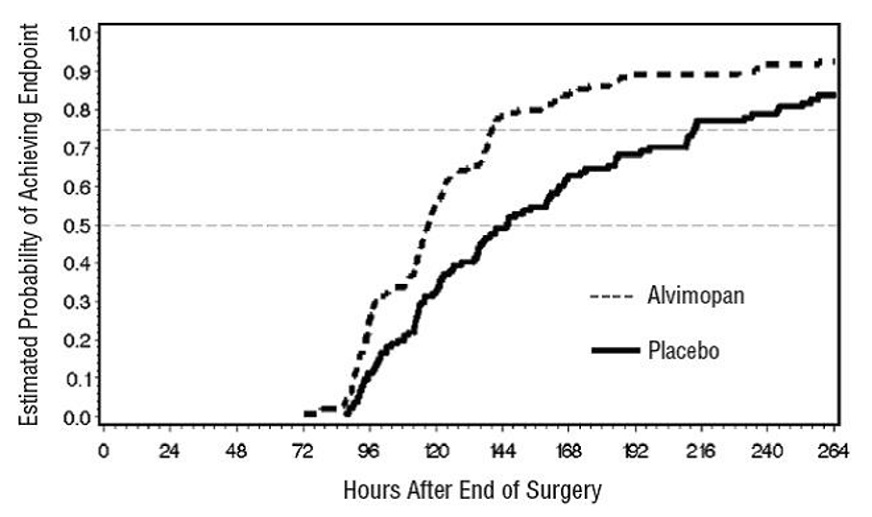 DRUG LABEL: Alvimopan
NDC: 51407-870 | Form: CAPSULE
Manufacturer: Golden State Medical Supply, Inc.
Category: prescription | Type: HUMAN PRESCRIPTION DRUG LABEL
Date: 20240208

ACTIVE INGREDIENTS: ALVIMOPAN 12 mg/1 1
INACTIVE INGREDIENTS: FD&C BLUE NO. 1; POLYETHYLENE GLYCOL 3350; GELATIN, UNSPECIFIED; SODIUM LAURYL SULFATE; TITANIUM DIOXIDE; AMMONIA; FERROSOFERRIC OXIDE; PROPYLENE GLYCOL; SHELLAC

HIGHLIGHTS OF PRESCRIBING INFORMATION

ALVIMOPAN CAPSULES. These highlights do not include all the information needed to use ALVIMOPAN CAPSULES safely and effectively. See full prescribing information for ALVIMOPAN CAPSULES.
ALVIMOPAN capsules, for oral use
Initial U.S. Approval: 2008

WARNING: POTENTIAL RISK OF MYOCARDIAL INFARCTION WITH LONG-TERM USE: FOR SHORT-TERM HOSPITAL USE ONLY

See full prescribing information for complete boxed warning.

- Increased incidence of myocardial infarction was seen in a clinical trial of patients taking alvimopan for long-term use. (5.1)
- Alvimopan capsules are available only through a restricted program for short-term use (15 doses) called the Alvimopan REMS Program. (5.1, 5.2)

1 INDICATIONS AND USAGE

Alvimopan capsules are an opioid antagonist indicated to accelerate the time to upper and lower gastrointestinal recovery following surgeries that include partial bowel resection with primary anastomosis. (1)

2 DOSAGE AND ADMINISTRATION

- For hospital use only. (2)
- The recommended dosage is 12 mg administered 30 minutes to 5 hours prior to surgery followed by 12 mg twice daily beginning the day after surgery until discharge for a maximum of 7 days. Patients should not receive more than 15 doses of alvimopan capsules. (2)

3 DOSAGE FORMS AND STRENGTHS

Capsules: 12 mg (3)

4 CONTRAINDICATIONS

Patients who have taken therapeutic doses of opioids for more than 7 consecutive days prior to taking alvimopan capsules. (4)

5 WARNINGS AND PRECAUTIONS

- Myocardial Infarction: A higher number of myocardial infarctions was reported in patients treated with alvimopan 0.5 mg twice daily compared with placebo in a 12-month study in patients treated with opioids for chronic non-cancer pain, although a causal relationship with long-term use has not been established. (5.1)
- Gastrointestinal Adverse Reactions in Opioid Tolerant Patients: Patients recently exposed to opioids may be more sensitive to the effects of alvimopan and experience gastrointestinal adverse reactions (e.g., abdominal pain, nausea and vomiting, and diarrhea). (5.3)
- Patients with Severe Hepatic Impairment: Increased risk of serious adverse reactions due to higher plasma concentrations; use is not recommended. (5.4, 8.6)
- Patients with End-Stage Renal Disease: No studies have been conducted; use is not recommended. (5.5, 8.7)
- Patients with Complete Gastrointestinal Obstruction: No studies have been conducted in patients with complete gastrointestinal obstruction or in patients who have surgery for correction of complete bowel obstruction; use is not recommended. (5.6)
- Patients with Pancreatic and Gastric Anastomoses: No studies have been conducted; use is not recommended. (5.7)

6 ADVERSE REACTIONS

Most common adverse reaction (≥1.5%): dyspepsia. (6.1)

To report SUSPECTED ADVERSE REACTIONS, contact Hikma Pharmaceuticals USA Inc. at 1-800-962-8364 or FDA at 1-800-FDA-1088 or www.fda.gov/medwatch.

8 USE IN SPECIFIC POPULATIONS

- Hepatic Impairment: Monitor patients with mild-to-moderate impairment for gastrointestinal adverse reactions. (8.6)
- Renal Impairment: Monitor patients with mild-to-severe impairment for gastrointestinal adverse reactions. (8.7)
- Race/Ethnicity: Monitor Japanese patients for gastrointestinal adverse reactions. (8.8)

FULL PRESCRIBING INFORMATION

WARNING: POTENTIAL RISK OF MYOCARDIAL INFARCTION WITH LONG-TERM USE: FOR SHORT-TERM HOSPITAL USE ONLY

There was a greater incidence of myocardial infarction in alvimopan-treated patients compared to placebo-treated patients in a 12-month clinical trial, although a causal relationship has not been established. In short-term trials with alvimopan, no increased risk of myocardial infarction was observed [see Warnings and Precautions (5.1)] .

Because of the potential risk of myocardial infarction with long-term use, alvimopan is available only through a restricted program for short-term use (15 doses) under a Risk Evaluation and Mitigation Strategy (REMS) called the Alvimopan REMS Program [see Warnings and Precautions (5.1, 5.2)] .

1 INDICATIONS AND USAGE

Alvimopan capsules are indicated to accelerate the time to upper and lower gastrointestinal recovery following surgeries that include partial bowel resection with primary anastomosis.

2 DOSAGE AND ADMINISTRATION

For hospital use only. The recommended adult dosage of alvimopan capsules is 12 mg administered 30 minutes to 5 hours prior to surgery followed by 12 mg twice daily beginning the day after surgery until discharge for a maximum of 7 days. Patients should not receive more than 15 doses of alvimopan capsules.

Alvimopan capsules can be taken with or without food [see Clinical Pharmacology (12.3)] .

3 DOSAGE FORMS AND STRENGTHS

12 mg blue, opaque hard gelatin capsules with “54 88” imprinted in black on both the body and the cap of the capsule.

4 CONTRAINDICATIONS

Alvimopan capsules are contraindicated in patients who have taken therapeutic doses of opioids for more than 7 consecutive days immediately prior to taking alvimopan capsules [see Warnings and Precautions (5.3)] .

5 WARNINGS AND PRECAUTIONS

5.1 Potential Risk of Myocardial Infarction with Long-Term Use

There were more reports of myocardial infarctions in patients treated with alvimopan 0.5 mg twice daily compared with placebo-treated patients in a 12-month study of patients treated with opioids for chronic non-cancer pain (alvimopan 0.5 mg, n = 538; placebo, n = 267). In this study, the majority of myocardial infarctions occurred between 1 and 4 months after initiation of treatment. This imbalance has not been observed in other studies of alvimopan in patients treated with opioids for chronic pain, nor in patients treated within the surgical setting, including patients undergoing surgeries that included bowel resection who received alvimopan 12 mg twice daily for up to 7 days (the indicated dose and patient population; alvimopan 12 mg, n = 1,142; placebo, n = 1,120). A causal relationship with alvimopan with long-term use has not been established.

Alvimopan capsules are available only through a program under a REMS that restricts use to enrolled hospitals [see Warnings and Precautions (5.2)] .

5.2 Alvimopan REMS Program

Alvimopan capsules are available only through a program called the Alvimopan REMS Program that restricts use to enrolled hospitals because of the potential risk of myocardial infarction with long-term use of alvimopan capsules [see Warnings and Precautions (5.1)] .

Notable requirements of the Alvimopan REMS Program include the following:

Alvimopan capsules are available only for short-term (15 doses) use in hospitalized patients. Only hospitals that have enrolled in and met all of the requirements for the Alvimopan REMS Program may use alvimopan capsules.

To enroll in the Alvimopan REMS Program, an authorized hospital representative must acknowledge that:

- hospital staff who prescribe, dispense, or administer alvimopan capsules have been provided the educational materials on the need to limit use of alvimopan capsules to short-term, inpatient use;
- patients will not receive more than 15 doses of alvimopan capsules; and
- alvimopan capsules will not be dispensed to patients after they have been discharged from the hospital.
- Further information is available at www.alvimopanREMS.com or 1-800-278-0340.

5.3 Gastrointestinal-Related Adverse Reactions in Opioid-Tolerant Patients

Patients recently exposed to opioids are expected to be more sensitive to the effects of mu-opioid receptor antagonists, such as alvimopan. Since alvimopan acts peripherally, clinical signs and symptoms of increased sensitivity would be related to the gastrointestinal tract (e.g., abdominal pain, nausea and vomiting, diarrhea). Patients receiving more than 3 doses of an opioid within the week prior to surgery were not studied in the postoperative ileus clinical trials. Therefore, if alvimopan is administered to these patients, they should be monitored for gastrointestinal adverse reactions. Alvimopan is contraindicated in patients who have taken therapeutic doses of opioids for more than 7 consecutive days immediately prior to taking alvimopan [see Contraindications (4)] .

5.4 Risk of Serious Adverse Reactions in Patients with Severe Hepatic Impairment

Patients with severe hepatic impairment may be at higher risk of serious adverse reactions (including dose-related serious adverse reactions) because up to 10-fold higher plasma concentrations of alvimopan have been observed in such patients compared with patients with normal hepatic function. Therefore, the use of alvimopan is not recommended in this population [see Use in Specific Populations (8.6)] .

5.5 End-Stage Renal Disease

No studies have been conducted in patients with end-stage renal disease. Alvimopan is not recommended for use in these patients [see Use in Specific Populations (8.7)] .

5.6 Risk of Serious Adverse Reactions in Patients with Complete Gastrointestinal Obstruction

No studies have been conducted in patients with complete gastrointestinal obstruction or in patients who have surgery for correction of complete bowel obstruction. Alvimopan is not recommended for use in these patients.

5.7 Risk of Serious Adverse Reactions in Pancreatic and Gastric Anastomoses

Alvimopan has not been studied in patients having pancreatic or gastric anastomosis. Therefore, alvimopan is not recommended for use in these patients.

6 ADVERSE REACTIONS

The following clinically significant adverse reactions are described elsewhere in the labeling:

- Potential Risk of Myocardial Infarction with Long-Term Use [see Warnings and Precautions (5.1)]
- Gastrointestinal-Related Adverse Reactions in Opioid-Tolerant Patients [see Warnings and Precautions (5.3)]
- Risk of Serious Adverse Reactions in Patients with Severe Hepatic Impairment [see Warnings and Precautions (5.4)]
- Risk of Serious Adverse Reactions in Patients with Complete Gastrointestinal Obstruction [see Warnings and Precautions (5.6)]
- Risk of Serious Adverse Reactions in Pancreatic and Gastric Anastomoses [see Warnings and Precautions (5.7)]

6.1 Clinical Trials Experience

Because clinical trials are conducted under widely varying conditions, adverse reaction rates observed in the clinical trials of a drug cannot be compared directly with rates in the clinical trials of another drug and may not reflect the rates observed in clinical practice. The adverse event information from clinical trials does, however, provide a basis for identifying the adverse events that appear to be related to drug use and for approximating rates.

The data described below reflect exposure to alvimopan 12 mg in 1,793 patients in 10 placebo-controlled studies. The population was 19 to 97 years old, 64% were female, and 84% were Caucasian; 64% were undergoing a surgery that included bowel resection. The first dose of alvimopan was administered 30 minutes to 5 hours before the scheduled start of surgery and then twice daily until hospital discharge (or for a maximum of 7 days of postoperative treatment).

Among alvimopan-treated patients undergoing surgeries that included a bowel resection, the most common adverse reaction (incidence ≥1.5%) occurring with a higher frequency than placebo was dyspepsia (alvimopan, 1.5%; placebo, 0.8%). Adverse reactions are events that occurred after the first dose of study medication treatment and within 7 days of the last dose of study medication or events present at baseline that increased in severity after the start of study medication treatment.

7 DRUG INTERACTIONS

7.1 Effects of Alvimopan on Intravenous Morphine

Coadministration of alvimopan does not appear to alter the pharmacokinetics of morphine and its metabolite, morphine-6-glucuronide, to a clinically significant degree when morphine is administered intravenously. Dosage adjustment for intravenously administered morphine is not necessary when it is coadministered with alvimopan.

7.2 Effects of Concomitant Acid Blockers or Antibiotics

A population pharmacokinetic analysis suggests that the pharmacokinetics of alvimopan were not affected by concomitant administration of acid blockers (proton pump inhibitors (PPIs), histamine-2 (H2) receptor antagonists) or antibiotics. No dosage adjustments are necessary in patients taking acid blockers or antibiotics with alvimopan.

8 USE IN SPECIFIC POPULATIONS

8.1 Pregnancy

Risk Summary:

Available data regarding use of alvimopan in pregnant women are limited, and are insufficient to inform a drug-associated risk of major birth defects, miscarriage or adverse maternal or fetal outcomes.

No fetal harm was observed in animal reproduction studies with oral administration of alvimopan during organogenesis to pregnant rats at doses 68 to 136 times the recommended human oral dose, or with intravenous administration during organogenesis to pregnant rats and pregnant rabbits at doses 3.4 to 6.8 times, and 5 to 10 times, respectively, the recommended human oral dose (see Data).

The estimated background risk of major birth defects and miscarriage for the indicated population is unknown. All pregnancies have a background risk of birth defect, loss, or other adverse outcomes. In the U.S. general population, the estimated background risk of major birth defects and miscarriage in clinically recognized pregnancies is 2% to 4% and 15% to 20%, respectively.

Data

Animal Data

Embryo-fetal studies were performed in pregnant rats during organogenesis (gestation days 7 through 19, or 20) at oral doses up to 200 mg/kg/day (about 68 to 136 times the recommended human oral dose based on body surface area) and at intravenous doses up to 10 mg/kg/day (about 3.4 to 6.8 times the recommended human oral dose based on body surface area). A study in pregnant rabbits during organogenesis (gestation days 6 through 18) at intravenous doses up to 15 mg/kg/day (about 5 to 10 times the recommended human oral dose based on body surface area) revealed no evidence of harm to the fetus due to alvimopan.

In an intravenous pre- and postnatal development study (gestation day 7 through lactation day 20) in rats, alvimopan did not cause any adverse effect on pre- and postnatal development at doses up to 10 mg/kg/day (about 6.8 times the recommended human oral dose based on body surface area).

8.2 Lactation

Risk Summary:

There are no data on the presence of alvimopan in human milk, the effects on the breastfed infant, or the effects on milk production. Alvimopan and its ‘metabolite’ are detected in the milk of lactating rats following intravenous administration (see Data). It is unknown if alvimopan is present in rat milk following oral administration.

The developmental and health benefits of breastfeeding should be considered along with the mother's clinical need for alvimopan and any potential adverse effects on the breastfed child from alvimopan or from the underlying maternal condition.

Data

Following intravenous administration of alvimopan to lactating rats at 10 mg/kg/day, concentrations of alvimopan and its ‘metabolite’ in the milk were approximately 15- and 0.11-fold, respectively, the concentration of alvimopan in maternal plasma at 1-hour post-dose.

8.4 Pediatric Use

Safety and effectiveness in pediatric patients have not been established.

8.5 Geriatric Use

Of the total number of patients in 6 clinical efficacy studies treated with alvimopan 12 mg or placebo, 46% were 65 years of age and over, while 18% were 75 years of age and over. No overall differences in safety or effectiveness were observed between these patients and younger patients, and other reported clinical experience has not identified differences in responses between the elderly and younger patients, but greater sensitivity of some older individuals cannot be ruled out. No dosage adjustment based on increased age is required [see Clinical Pharmacology (12.3)] .

8.6 Hepatic Impairment

Alvimopan is not recommended for use in patients with severe hepatic impairment.

Dosage adjustment is not required for patients with mild-to-moderate hepatic impairment. Patients with mild-to-moderate hepatic impairment should be closely monitored for possible adverse reactions (e.g., diarrhea, gastrointestinal pain, cramping) that could indicate high alvimopan or ‘metabolite’ concentrations, and alvimopan should be discontinued if adverse reactions occur [see Warnings and Precautions (5.4), Clinical Pharmacology (12.3)] .

8.7 Renal Impairment

Alvimopan is not recommended for use in patients with end-stage renal disease. Dosage adjustment is not required for patients with mild-to-severe renal impairment, but they should be monitored for adverse reactions. Patients with severe renal impairment should be closely monitored for possible adverse reactions (e.g., diarrhea, gastrointestinal pain, cramping) that could indicate high alvimopan or ‘metabolite’ concentrations, and alvimopan should be discontinued if adverse reactions occur [see Clinical Pharmacology (12.3)] .

8.8 Race/Ethnicity

No dosage adjustment is necessary in Black, Hispanic, and Japanese patients. However, the exposure to alvimopan in Japanese healthy male subjects was approximately 2-fold greater than in Caucasian subjects. Japanese patients should be closely monitored for possible adverse reactions (e.g., diarrhea, gastrointestinal pain, cramping) that could indicate high alvimopan or ‘metabolite’ concentrations, and alvimopan should be discontinued if adverse reactions occur [see Clinical Pharmacology (12.3)] .

11 DESCRIPTION

Alvimopan capsules contain alvimopan, an opioid antagonist. Chemically, alvimopan is the single stereoisomer [[2(S)-[[4(R)-(3-hydroxyphenyl)-3(R),4-dimethyl-1-piperidinyl]methyl]-1-oxo-3-phenylpropyl]amino]acetic acid dihydrate. It has the following structural formula:

Alvimopan is a white to light beige powder with a molecular weight of 460.6, and the empirical formula is C25H32N2O4•2H2O. It has a solubility of <0.1 mg/mL in water or buffered solutions between pH 3.0 and 9.0, 1 to 5 mg/mL in buffered solutions at pH 1.2, and 10 to 25 mg/mL in aqueous 0.1 N sodium hydroxide. At physiological pH, alvimopan is zwitterionic, a property that contributes to its low solubility.

Alvimopan capsules for oral administration contain 12 mg of alvimopan on an anhydrous basis suspended in the inactive ingredient polyethylene glycol 3350. The capsule shell contains FD&C Blue 1, gelatin, sodium lauryl sulfate, and titanium dioxide. The black ink contains ammonium hydroxide, ferrosoferric oxide, propylene glycol, and shellac.

12 CLINICAL PHARMACOLOGY

12.1 Mechanism of Action

Alvimopan is a selective antagonist of the cloned human µ-opioid receptor with a Ki of 0.4 nM (0.2 ng/mL) and no measurable opioid-agonist effects in standard pharmacologic assays. The dissociation of [^3H]-alvimopan from the human µ-opioid receptor is slower than that of other opioid ligands, consistent with its higher affinity for the receptor. At concentrations of 1 to 10 µM, alvimopan demonstrated no activity at any of over 70 non-opioid receptors, enzymes, and ion channels.

Postoperative ileus is the impairment of gastrointestinal motility after intra-abdominal surgery or other, non-abdominal surgeries. Postoperative ileus affects all segments of the gastrointestinal tract and may last from 5 to 6 days, or even longer. This may potentially delay gastrointestinal recovery and hospital discharge until its resolution. It is characterized by abdominal distention and bloating, nausea, vomiting, pain, accumulation of gas and fluids in the bowel, and delayed passage of flatus and defecation. Postoperative ileus is the result of a multifactorial process that includes inhibitory sympathetic input and release of hormones, neurotransmitters, and other mediators (e.g., endogenous opioids). A component of postoperative ileus also results from an inflammatory reaction and the effects of opioid analgesics. Morphine and other µ-opioid receptor agonists are universally used for the treatment of acute postsurgical pain; however, they are known to have an inhibitory effect on gastrointestinal motility and may prolong the duration of postoperative ileus.

Following oral administration, alvimopan antagonizes the peripheral effects of opioids on gastrointestinal motility and secretion by competitively binding to gastrointestinal tract µ-opioid receptors. The antagonism produced by alvimopan at opioid receptors is evident in isolated guinea pig ileum preparations in which alvimopan competitively antagonizes the effects of morphine on contractility. Alvimopan achieves this selective gastrointestinal opioid antagonism without reversing the central analgesic effects of µ-opioid agonists.

12.2 Pharmacodynamics

In an exploratory study in healthy subjects, alvimopan 12 mg administered twice a day reduced the delay in small and large bowel transit induced by codeine 30 mg administered 4 times a day, as measured by gastrointestinal scintigraphy. In the same study, concomitant alvimopan did not reduce the delay in gastric emptying induced by codeine.

Cardiac Electrophysiology:

At a dosage of 24 mg twice daily (two times the approved recommended dosage) for 7 days, alvimopan does not prolong the QT interval to any clinically relevant extent. The potential for QTc effects at higher doses has not been studied.

12.3 Pharmacokinetics

Following oral administration of alvimopan, an amide hydrolysis compound is present in the systemic circulation, which is considered a product exclusively of intestinal flora metabolism. This compound is referred to as the ‘metabolite’. It is also a mu-opioid receptor antagonist with a Ki of 0.8 nM (0.3 ng/mL).

Absorption:

Following oral administration of alvimopan capsules in healthy plasma subjects, the alvimopan concentration peaked at approximately 2 hours post-dose. No significant accumulation in the concentration of alvimopan was observed following twice daily dosing. The mean peak plasma concentration was 10.98 (±6.43) ng/mL and mean AUC0-12hwas 40.2 (±22.5) ng•h/mL after dosing of alvimopan at 12 mg twice daily for 5 days. The absolute bioavailability was estimated to be 6% (range, 1% to 19%). There was a delay in the appearance of the ‘metabolite’, which had a median Tmaxof 36 hours following administration of a single dose of alvimopan. Concentrations of the ‘metabolite’ were highly variable between subjects and within a subject. The ‘metabolite’ accumulated after multiple doses of alvimopan. The mean Cmaxfor the ‘metabolite’ after alvimopan 12 mg twice daily for 5 days was 35.73 ± 35.29 ng/mL.

Concentrations of alvimopan and its ‘metabolite’ are higher (approximately 1.9-fold and 1.4-fold, respectively) in postoperative ileus patients than in healthy subjects.

Effect of Food:A high-fat meal decreased the extent and rate of alvimopan absorption. The Cmaxand AUC were decreased by approximately 38% and 21%, respectively, and the Tmaxwas prolonged by approximately 1 hour. The clinical significance of this decreased bioavailability is unknown. In postoperative ileus clinical trials, the preoperative dose of alvimopan was administered in a fasting state. Subsequent doses were given without regard to meals.

Distribution:

The steady-state volume of distribution of alvimopan was estimated to be 30±10 L. Plasma protein binding of alvimopan and its ‘metabolite’ was independent of concentration over ranges observed clinically and averaged 80% and 94%, respectively. Both alvimopan and the ‘metabolite’ were bound to albumin and not to alpha-1 acid glycoprotein.

Elimination:

Metabolism and Excretion: In vitrodata suggest that alvimopan is not a substrate of CYP enzymes. The average plasma clearance for alvimopan was 402 (±89) mL/min. Renal excretion accounted for approximately 35% of total clearance. There was no evidence that hepatic metabolism was a significant route for alvimopan elimination. Biliary secretion was considered the primary pathway for alvimopan elimination. Unabsorbed drug and unchanged alvimopan resulting from biliary excretion were then hydrolyzed to its ‘metabolite’ by gut microflora. The ‘metabolite’ was eliminated in the feces and in the urine as unchanged ‘metabolite’, the glucuronide conjugate of the ‘metabolite’, and other minor metabolites. The mean terminal phase half-life of alvimopan after multiple oral doses of alvimopan ranged from 10 to 17 hours. The terminal half-life of the ‘metabolite’ ranged from 10 to 18 hours.

Specific Populations:

Geriatric Patients:The pharmacokinetics of alvimopan, but not its ‘metabolite’, were related to age, but this effect was not clinically significant and does not warrant dosage adjustment based on increased age.

Racial or Ethnic Groups:The pharmacokinetic characteristics of alvimopan were not affected by Hispanic or Black race. Plasma ‘metabolite’ concentrations were lower in Black and Hispanic patients (by 43% and 82%, respectively) than in Caucasian patients following alvimopan administration. These changes are not considered to be clinically significant in surgical patients. Japanese healthy male subjects had an approximately 2-fold increase in plasma alvimopan concentrations, but no change in ‘metabolite’ pharmacokinetics. The pharmacokinetics of alvimopan have not been studied in subjects of other East Asian ancestry. Dosage adjustment in Japanese patients is not required [see Use in Specific Populations (8.8)] .

Male and Female Patients:There was no effect of sex on the pharmacokinetics of alvimopan or the ‘metabolite’.

Patients with Hepatic Impairment:Exposure to alvimopan following a single 12 mg dose tended to be higher (1.5- to 2-fold, on average) in patients with mild or moderate hepatic impairment (as defined by Child-Pugh Class A and B, n = 8 each) compared with healthy controls (n = 4). There were no consistent effects on the Cmaxor half-life of alvimopan in patients with hepatic impairment. However, 2 of 16 patients with mild-to-moderate hepatic impairment had longer than expected half-lives of alvimopan, indicating that some accumulation may occur upon multiple dosing. The Cmaxof the ‘metabolite’ tended to be more variable in patients with mild or moderate hepatic impairment than in matched normal subjects. A study of 3 patients with severe hepatic impairment (Child-Pugh Class C), indicated similar alvimopan exposure in 2 patients and an approximately 10-fold increase in Cmaxand exposure in 1 patient with severe hepatic impairment when compared with healthy controls [see Warnings and Precautions (5.4), Use in Specific Populations (8.6)] .

Patients with Renal Impairment:There was no relationship between renal function (i.e., creatinine clearance [CrCl]) and plasma alvimopan pharmacokinetics (Cmax, AUC, or half-life) in patients with mild (CrCl 51 to 80 mL/min), moderate (CrCl 31 to 50 mL/min), or severe (CrCl less than 30 mL/min) renal impairment (n = 6 each). Renal clearance of alvimopan was related to renal function; however, because renal clearance was only a small fraction (35%) of the total clearance, renal impairment had a small effect on the apparent oral clearance of alvimopan. The half-lives of alvimopan were comparable in the mild, moderate, and control renal impairment groups but longer in the severe renal impairment group. Exposure to the ‘metabolite’ tended to be 2- to 5-fold higher in patients with moderate or severe renal impairment compared with patients with mild renal impairment or control subjects. Thus, there may be accumulation of alvimopan and ‘metabolite’ in patients with severe renal impairment receiving multiple doses of alvimopan. Patients with end-stage renal disease were not studied [see Warnings and Precautions (5.5), Use in Specific Populations (8.7)] .

Patients with Crohn’s Disease:There was no relationship between disease activity in patients with Crohn’s disease (measured as Crohn’s Disease Activity Index or bowel movement frequency) and alvimopan pharmacokinetics (AUC or Cmax). Patients with active or quiescent Crohn’s disease had increased variability in alvimopan pharmacokinetics, and exposure tended to be 2-fold higher in patients with quiescent disease than in those with active disease or in normal subjects. Concentrations of the ‘metabolite’ were lower in patients with Crohn’s disease.

Drug Interaction Studies:

Potential for Drugs to Affect Alvimopan Pharmacokinetics:Concomitant administration of alvimopan with inducers or inhibitors of CYP enzymes is unlikely to alter the metabolism of alvimopan because alvimopan is metabolized mainly by non-CYP enzyme pathway. No clinical studies have been performed to assess the effect of concomitant administration of inducers or inhibitors of cytochrome P450 enzymes on alvimopan pharmacokinetics.

In vitrostudies suggest that alvimopan and its ‘metabolite’ are substrates for p-glycoprotein. A population pharmacokinetic analysis did not reveal any evidence that alvimopan or ‘metabolite’ pharmacokinetics were influenced by concomitant medications that are mild-to-moderate p-glycoprotein inhibitors. No clinical studies of concomitant administration of alvimopan and strong inhibitors of p-glycoprotein (e.g., verapamil, cyclosporine, amiodarone, itraconazole, quinine, spironolactone, quinidine, diltiazem, bepridil) have been conducted.

A population pharmacokinetic analysis suggests that the pharmacokinetics of alvimopan were not affected by concomitant administration of acid blockers or antibiotics. However, plasma concentrations of the ‘metabolite’ were lower in patients receiving acid blockers or preoperative oral antibiotics (49% and 81%, respectively). No dosage adjustments are necessary in these patients.

Potential for Alvimopan to Affect the Pharmacokinetics of Other Drugs:Alvimopan and its ‘metabolite’ are not inhibitors of CYP 1A2, 2C9, 2C19, 3A4, 2D6, and 2E1 in vitroat concentrations far in excess of those observed clinically.

Alvimopan and its ‘metabolite’ are not inducers of CYP 1A2, 2B6, 2C9, 2C19, and 3A4.

In vitrostudies also suggest that alvimopan and its ‘metabolite’ are not inhibitors of p-glycoprotein.

These in vitrofindings suggest that alvimopan is unlikely to alter the pharmacokinetics of coadministered drugs through inhibition or induction of CYP enzymes or inhibition of p-glycoprotein.

13 NONCLINICAL TOXICOLOGY

13.1 Carcinogenesis, Mutagenesis, Impairment of Fertility

Carcinogenesis:Two-year carcinogenicity studies were conducted with alvimopan in CD-1 mice at oral doses up to 4000 mg/kg/day and in Sprague Dawley®rats at oral doses up to 500 mg/kg/day. Oral administration of alvimopan for 104 weeks produced significant increases in the incidences of fibroma, fibrosarcoma, and sarcoma in the skin/subcutis, and of osteoma/osteosarcoma in bones of female mice at 4000 mg/kg/day (about 674 times the recommended human dose based on body surface area). In rats, oral administration of alvimopan for 104 weeks did not produce any tumor up to 500 mg/kg/day (about 166 times the recommended human dose based on body surface area).

Mutagenesis:Alvimopan was not genotoxic in the Ames test, the mouse lymphoma cell (L5178Y/TK+/−) forward mutation test, the Chinese Hamster Ovary (CHO) cell chromosome aberration test, or the mouse micronucleus test. The pharmacologically active ‘metabolite’ was negative in the Ames test, chromosome aberration test in CHO cells, and mouse micronucleus test.

Impairment of Fertility:Alvimopan at intravenous doses up to 10 mg/kg/day (about 3.4 to 6.8 times the recommended human oral dose based on body surface area) was found to have no adverse effect on fertility and reproductive performance of male or female rats.

14 CLINICAL STUDIES

The efficacy of alvimopan in the management of postoperative ileus was evaluated in 6 multicenter, randomized, double-blind, parallel-group, placebo-controlled studies: 5 U.S. studies (Studies 1 to 4 and 6) and 1 non-U.S. study (Study 5). Patients 18 years of age or older undergoing partial large or small bowel resection surgery with primary anastomosis for colorectal or small bowel disease, total abdominal hysterectomy, or radical cystectomy for bladder cancer (in this procedure, resected segments of bowel are used for reconstruction of the urinary tract) under general anesthesia were randomly assigned to receive oral doses of alvimopan 12 mg or matching placebo. The initial dose was administered at least 30 minutes and up to 5 hours prior to the scheduled start of surgery for most patients, and subsequent doses were administered twice daily beginning on the first postoperative day and continued until hospital discharge or a maximum of 7 days. There were no limitations on the type of general anesthesia used, but intrathecal or epidural opioids or anesthetics were prohibited.

All patients in the U.S. studies were scheduled to receive intravenous patient-controlled opioid analgesia. In the non-U.S. study, patients were scheduled to receive opioids either by intravenous patient-controlled opioid analgesia or bolus parenteral administration (intravenous or intramuscular). In all studies, there was no restriction on the type of opioid used or the duration of intravenous patient-controlled opioid analgesia. A standardized accelerated postoperative care pathway was implemented: early nasogastric tube removal (before the first postoperative dose); early ambulation (day following surgery); early diet advancement (liquids offered the day following surgery for patients undergoing bowel resection and by the third day following surgery for patients undergoing radical cystectomy; solids by the second day following surgery for patients undergoing bowel resection and by the fourth day following surgery for patients undergoing radical cystectomy), as tolerated.

Patients who received more than 3 doses of an opioid (regardless of route) during the 7 days prior to surgery and patients with complete bowel obstruction or who were scheduled for a total colectomy, colostomy, or ileostomy were excluded.

The primary endpoint for all studies was time to achieve resolution of postoperative ileus, a clinically defined composite measure of both upper and lower gastrointestinal recovery. Although both 2-component (GI2: toleration of solid food and first bowel movement) and 3-component (GI3: toleration of solid food and either first flatus or bowel movement) endpoints were used in all studies, GI2 is presented as it represents the most objective and clinically relevant measure of treatment response in patients undergoing surgeries that include a bowel resection. The time from the end of surgery to when the discharge order was written represented the length of hospital stay. In the 6 studies, 1,058 patients who underwent a surgery that included a bowel resection received placebo (not including 157 for total abdominal hysterectomy) and 1,096 patients received alvimopan 12 mg (not including 143 for total abdominal hysterectomy).

The efficacy of alvimopan following total abdominal hysterectomy has not been established. Therefore, the following data are presented only for surgeries that included a bowel resection (i.e., bowel resection or radical cystectomy).

Bowel Resection or Radical Cystectomy: A total of 2,154 patients underwent a surgery that included a bowel resection. The average age was 62 years, 54% were males, and 89% were Caucasian. The most common indications for surgery were colon or rectal cancer/malignancy, bladder cancer, and diverticular disease. In the non-U.S. bowel resection study (Study 5), average daily postoperative opioid consumption was approximately 50% lower and the use of non-opioid analgesics substantially higher, as compared with the U.S. bowel resection studies (Studies 1 to 4) for both treatment groups. During the first 48 hours postoperatively, the use of non-opioid analgesics was 69% compared with 4% for the non-U.S. and U.S. bowel resection studies, respectively. In each of the 6 studies, alvimopan accelerated the time to recovery of gastrointestinal function, as measured by the composite endpoint GI2, and time to discharge order written as compared with placebo. Hazard ratios greater than 1 indicate a higher probability of achieving the event during the study period with treatment with alvimopan than with placebo. Table 1 provides the Hazard Ratios, Kaplan Meier means, medians, and mean and median treatment differences (hours) in gastrointestinal recovery between alvimopan and placebo.

Table 1: GI2 Recovery (Hours) in Bowel Resection Patients
Study No.* | Alvimopan 12 mg |  | Placebo |  | Treatment Difference |  | Hazard Ratio (95% CI)
Study No.* | Mean† | Median | Mean† | Median | Means† | Medians | Hazard Ratio (95% CI)
1 | 92.0 | 80.0 | 111.8 | 96.6 | 19.8 | 16.6 | 1.533 (1.293, 1.816)
2 | 105.9 | 98.0 | 132.0 | 115.2 | 26.1 | 17.2 | 1.625; (1.256, 2.102)
3 | 116.4 | 101.8 | 130.3 | 116.8 | 14.0 | 15.0 | 1.365; (1.057, 1.764)
4 | 106.7 | 101.4 | 119.9 | 113.3 | 13.2 | 11.9 | 1.400; (1.035, 1.894)
5 | 98.2 | 92.8 | 108.8 | 95.9 | 10.6 | 3.1 | 1.299; (1.070, 1.575)
6 | 132.7 | 117.0 | 164.2 | 145.6 | 31.5 | 28.5 | 1.773; (1.359, 2.311)

* Study 1 = 14CL314; Study 2 = 14CL313; Study 3 = 14CL308; Study 4 = 14CL302; Study 5 = SB-767905/001; Study 6 = 14CL403

†The estimates of the means and differences of treatment means are biased because of the censoring of events not achieved prior to the end of the observation period (10 days). The estimates of the differences of treatment means are likely to be underestimates.

The Kaplan Meier estimate probabilities of patients receiving alvimopan who achieved GI2 were numerically higher at all times throughout the study observation period compared with those of patients receiving placebo (see Figures 1 and 2).

Figure 1: Time to GI2 Based on Results from Studies 1 through 5

Figure 2: Time to GI2 Based on Results from Study 6

In Studies 1 to 4, the differences between alvimopan and placebo patient groups in median time to ‘discharge order written’ ranged from 6 to 22 hours, in favor of alvimopan patients. The group differences in mean time to ‘discharge order written’ ranged from 13 to 21 hours. In Study 6, the median time difference was 19 hours in favor of alvimopan patients (mean time difference 22 hours).

Alvimopan did not reverse opioid analgesia as measured by visual analog scale pain intensity scores and/or amount of postoperative opioids administered across all 6 studies.

There were no sex-, age-, or race-related differences in treatment effect.

The incidence of anastomotic leak was low and comparable in patients receiving either alvimopan or placebo (0.7% and 1.0%, respectively).

16 HOW SUPPLIED/STORAGE AND HANDLING

Alvimopan capsules, 12 mg, are blue, opaque hard gelatin capsules with “54 88” imprinted in black on both the body and the cap of the capsule. Alvimopan capsules are available in unit-dose packs of 30 capsules (30 doses) (NDC 51407-870-33) for hospital use only.

Store at 25°C (77°F); excursions permitted to 15°C to 30°C (59°F to 86°F) [see USP Controlled Room Temperature].

17 PATIENT COUNSELING INFORMATION

Recent Use of Opioids:

Inform patients that they must disclose long-term or intermittent opioid pain therapy to their healthcare provider, including any use of opioids in the week prior to receiving alvimopan. Inform patients that recent use of opioids may make them more susceptible to adverse reactions to alvimopan, primarily those limited to the gastrointestinal tract (e.g., abdominal pain, nausea and vomiting, diarrhea).

Hospital Use Only:

Inform patients that alvimopan capsules are available only through a program called the Alvimopan REMS Program under a REMS that restricts use to enrolled hospitals because of the potential risk of myocardial infarction with long-term use of alvimopan. Alvimopan capsules are for hospital use only for no more than 7 days after their bowel resection surgery.

Most Common Adverse Reaction:

Inform patients that the most common adverse reaction with alvimopan in patients undergoing surgeries that include bowel resection is dyspepsia.

Brands listed are the trademarks of their respective owners.

Distributed by:

Hikma Pharmaceuticals USA Inc.

Berkeley Heights, NJ 07922

C50001264/01

Revised October 2022

Marketed by:

GSMS, Inc.

Camarillo, CA 93012 USA

PACKAGE/LABEL PRINCIPAL DISPLAY PANEL

NDC51407-870-33 30 (5x6) Unit-Dose Capsules
Alvimopan
Capsules
12 mg
HOSPITAL USE ONLY
Rx only